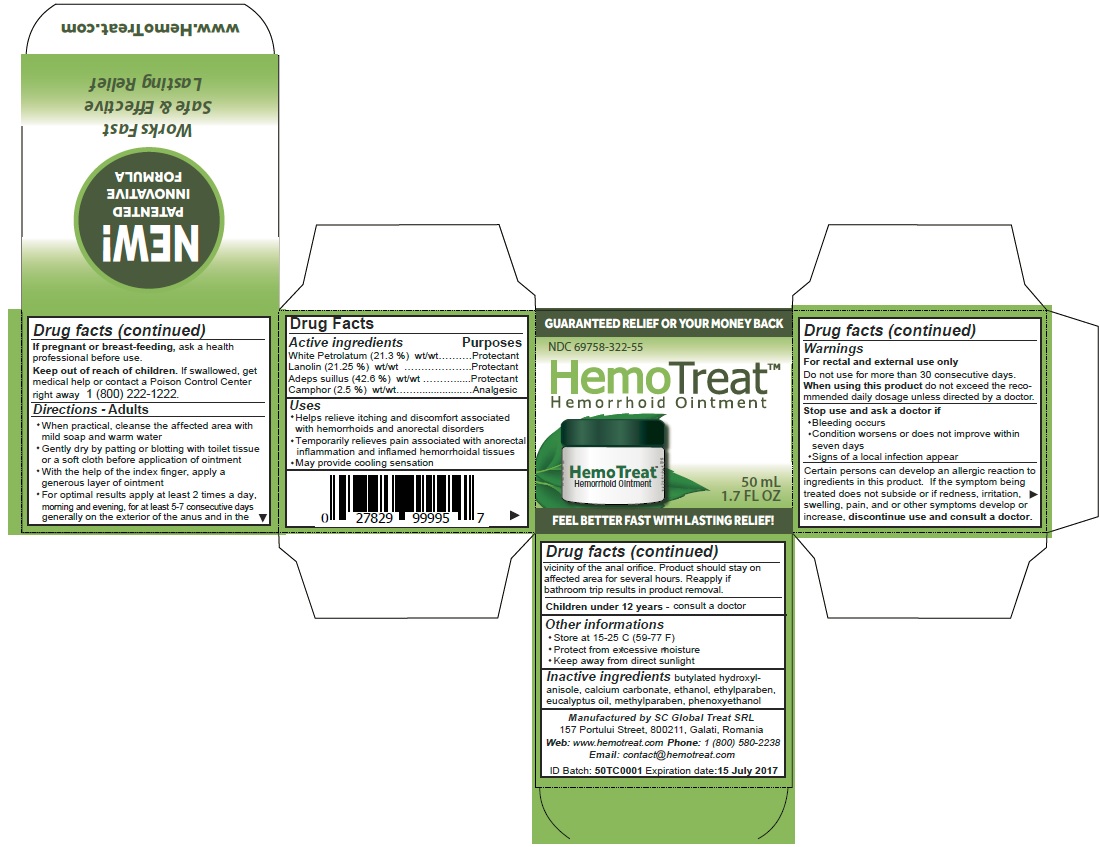 DRUG LABEL: HemoTreat
NDC: 69758-322 | Form: CREAM
Manufacturer: Global Treat srl
Category: otc | Type: HUMAN OTC DRUG LABEL
Date: 20210527

ACTIVE INGREDIENTS: PETROLATUM 0.213 g/1 g; LANOLIN 0.212 g/1 g; FAT, HARD 0.426 g/1 g; CAMPHOR (SYNTHETIC) 0.025 g/1 g
INACTIVE INGREDIENTS: BUTYLATED HYDROXYANISOLE; CALCIUM CARBONATE; ALCOHOL; ETHYLPARABEN; EUCALYPTUS OIL; METHYLPARABEN; PHENOXYETHANOL

HemoTreat (69758-322)

Active Ingredients

White Petrolatum 21.3% wt/wt

Lanolin 21.25% wtwt

Hard Fat 42.6% wt/wt

Camphor 2.5% wt/wt

Purposes

Protectant

Protectant

Protectant

Analgesic

Uses

- helps relieve itching and discomfort associated with hemorrhoids and anorectal disorders
- temporarily relieves pain associated with anorectal inflammation and inflamed hemorrhoidal tissues
- may provide cooling sensation

Warnings

For rectal use only

- Do not use for more than 30 days
- When using this product do not exceed the recommended daily dosage, unless directed by a doctor

Stop use and ask a doctor if:

- bleeding occurs
- condition worsens or does not improve within seven days
- signs of a local infection appear
- Certain person can develop allergic reactions to ingredients in this product. If the symptom being treated does not subside of if redness, irritation, swelling, pain, and or other symptoms develop or increase, discontinue use and consult a doctor.

PREGNANCY OR BREAST FEEDING

If pregnant or breast-feeding, ask a health professional before use.

KEEP OUT OF REACH OF CHILDREN

Keep out of the reach of children. If swallowed, get medical help or contact a poison Control Center right away 1 (800) 222-1222.

Directions

Adults

- when practical, cleanse the affected area with mild soap and warm water
- gently dry by patting or blotting with toilet tissue or a soft cloth before application of ointment
- with the help of the index finger, apply a thin layer of ointment
- apply 2 times a day, morning and evening, for 5-7 days. Spread on to the affected area, generally on the exterior of the anus and in the vicinity of the anal orifice

Children under 12 years

- consult a doctor

Other Information

- store at 15-25°C (59-77°F)
- protect from excessive moisture
- keep away from direct sunlight

Inactive Ingredients

butylated hydroxyl anisole, calcium carbonate, ethanol, ethylparaben, eucalyptus oil, methylparaben, phenoxyethanol

QUESTIONS

Manufactured by SC Global Treat SRL

157 Portului Street, 800211, Galati, Romania

Web: www.hemotreat.com

EMail: contact@hemotreat.com

Questions? Call: 1 (800) 580-2238

Principal Display Panel

NDC 69758-322-55

HemoTreat

Hemorrhoidal Ointment

H

50 ml